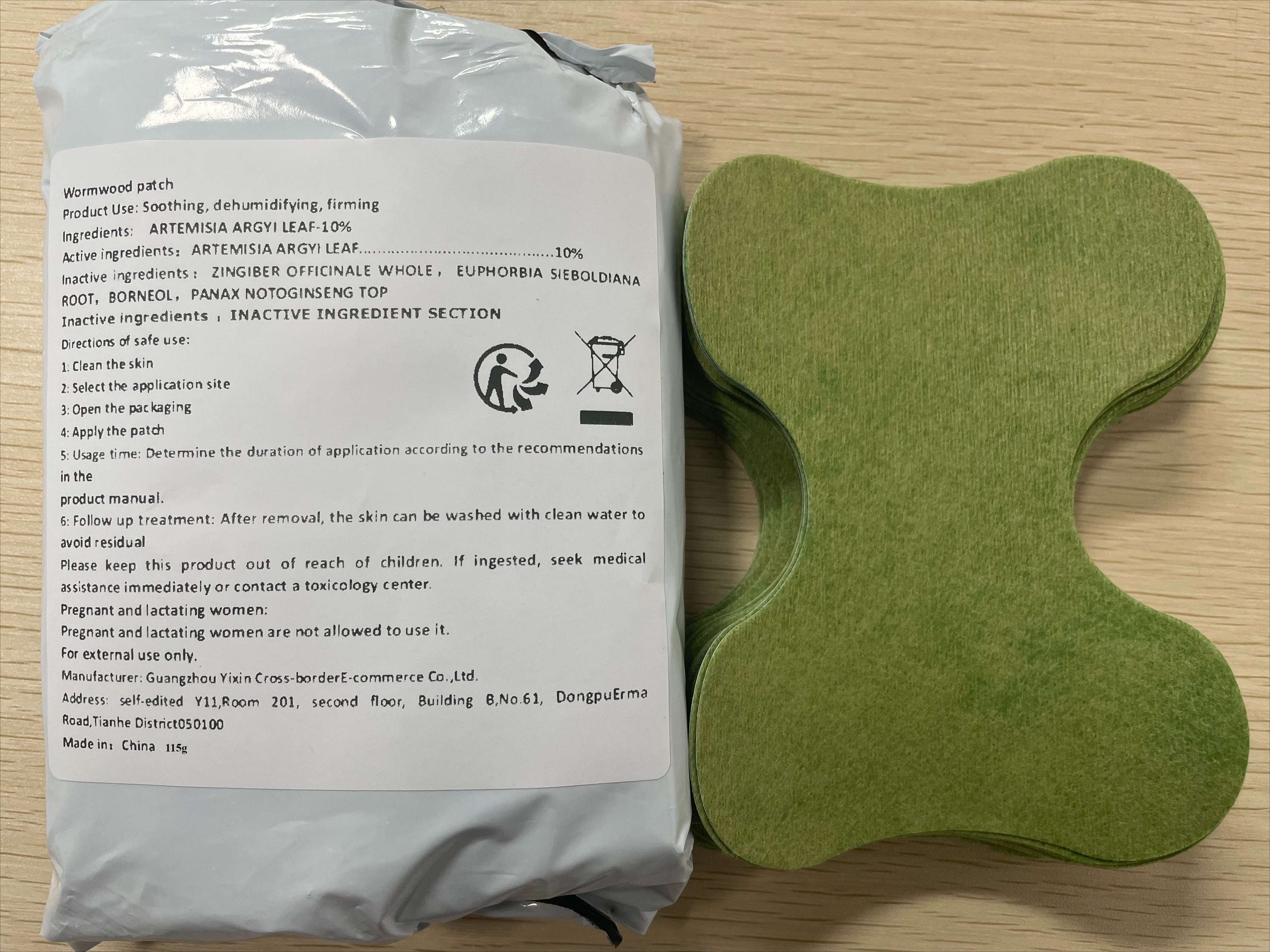 DRUG LABEL: Wormwood patch
NDC: 84778-011 | Form: SALVE
Manufacturer: Guangzhou Yixin Cross-border E-commerce Co., Ltd.
Category: otc | Type: HUMAN OTC DRUG LABEL
Date: 20241010

ACTIVE INGREDIENTS: ARTEMISIA ARGYI LEAF 10 g/100 g
INACTIVE INGREDIENTS: PANAX NOTOGINSENG TOP; ZINGIBER OFFICINALE WHOLE; BORNEOL; EUPHORBIA SIEBOLDIANA ROOT

Active ingredients

ARTEMISIA ARGYI LEAF-10%

Purpose

Relieve joint pain: Ai Cao Tie is often used to relieve joint pain caused by rheumatism, arthritis, or other reasons.

Improving muscle pain: For problems such as muscle soreness, sprains, strains, etc., mugwort patches can also have a certain soothing effect.

Promote blood circulation: Ai Cao Tie can help improve local blood circulation and promote smooth circulation of qi and blood.

Expelling Cold and Dampness: In traditional Chinese medicine theory, mugwort has the effect of dispelling cold and dampness, and is suitable for discomfort caused by cold and dampness

Uses

1: Clean the skin

2: Select the application site

3: Open the packaging

4: Apply the patch

5: Usage time: Determine the duration of application according to the recommendations in the product manual.

6: Follow up treatment: After removal, the skin can be washed with clean water to avoid residual

Warnings

Avoid damaging the skin:

Do not use mugwort patches on wounds, burns, damaged or inflamed skin. This may worsen skin problems or cause infections.

Avoid contact with eyes and mucous membranes:

Avoid allowing the patch to come into contact with mucous membranes such as the eyes and nose during use. If accidentally touched, please rinse immediately with plenty of water and seek medical assistance.

Notice for Children's Use:

Children should use it under adult supervision. Ensure that children do not accidentally consume the patch and avoid placing it in areas that are not easily accessible to children.

Long term use instructions:

Avoid prolonged continuous use, especially in the same area. Long term use may cause skin allergies or other adverse reactions.

Storage conditions:

It should be stored according to the instructions in the product manual, usually in a cool and dry place, away from direct sunlight and high temperature environments.

Pregnant and lactating women:

Pregnant and lactating women are not allowed to use it.

Dosage and administration

For external use only.

Do not use

Avoid damaging the skin:

Do not use mugwort patches on wounds, burns, damaged or inflamed skin. This may worsen skin problems or cause infections.

Avoid contact with eyes and mucous membranes:

Avoid allowing the patch to come into contact with mucous membranes such as the eyes and nose during use. If accidentally touched, please rinse immediately with plenty of water and seek medical assistance.

Notice for Children's Use:

Children should use it under adult supervision. Ensure that children do not accidentally consume the patch and avoid placing it in areas that are not easily accessible to children.

Long term use instructions:

Avoid prolonged continuous use, especially in the same area. Long term use may cause skin allergies or other adverse reactions.

Storage conditions:

It should be stored according to the instructions in the product manual, usually in a cool and dry place, away from direct sunlight and high temperature environments.

Pregnant and lactating women:

Pregnant and lactating women are not allowed to use it.

When using section

1: Clean the skin

2: Select the application site

3: Open the packaging

4: Apply the patch

5: Usage time: Determine the duration of application according to the recommendations in the product manual.

6: Follow up treatment: After removal, the skin can be washed with clean water to avoid residual

stop use

on broken or irritated scalp

Keep out of reach of children.

Please keep this product out of reach of children. If ingested, seek medical assistance immediately or contact a toxicology center.

Inactive ingredients

ZINGIBER OFFICINALE WHOLE，EUPHORBIA SIEBOLDIANA ROOT，BORNEOL，PANAX NOTOGINSENG TOP